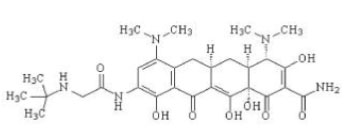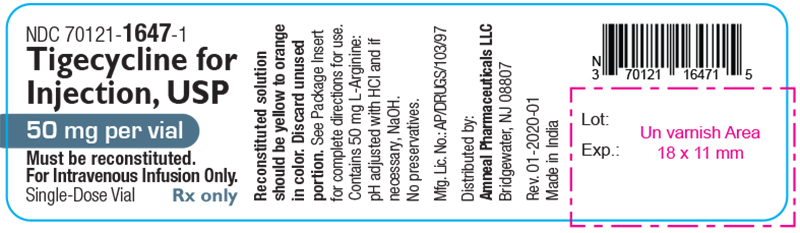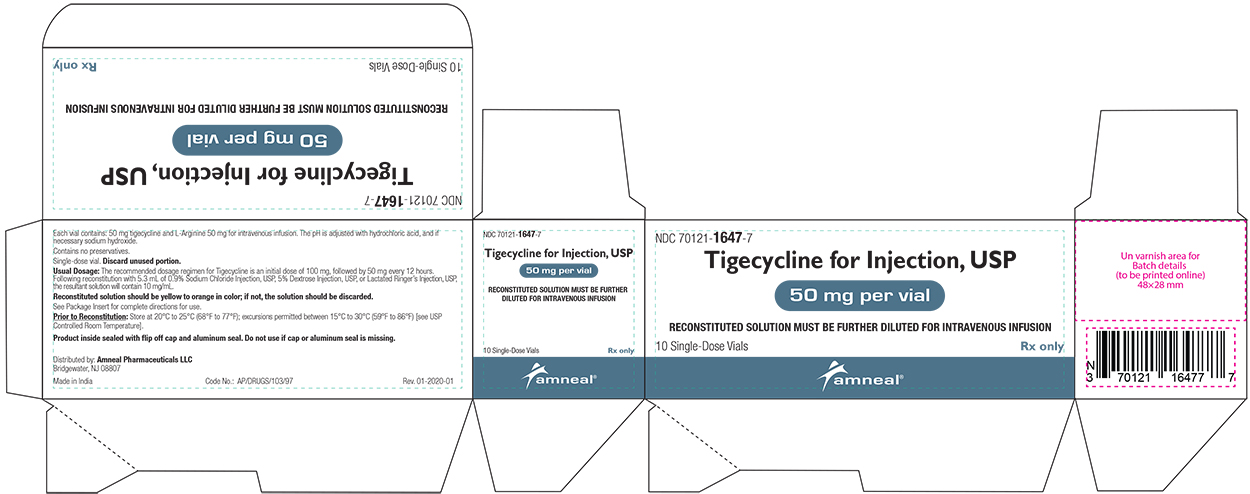 DRUG LABEL: Tigecycline
NDC: 70121-1647 | Form: INJECTION, POWDER, LYOPHILIZED, FOR SOLUTION
Manufacturer: Amneal Pharmaceuticals LLC
Category: prescription | Type: HUMAN PRESCRIPTION DRUG LABEL
Date: 20241217

ACTIVE INGREDIENTS: TIGECYCLINE 50 mg/5 mL
INACTIVE INGREDIENTS: HYDROCHLORIC ACID; SODIUM HYDROXIDE

HIGHLIGHTS OF PRESCRIBING INFORMATION

These highlights do not include all the information needed to use TIGECYCLINE FOR INJECTION safely and effectively. See full prescribing information for TIGECYCLINE FOR INJECTION.
TIGECYCLINE for injection, for intravenous use
Initial U.S. Approval: 2005

RECENT MAJOR CHANGES

Warnings and Precautions, Tetracycline-Class Adverse Effects (5.11) 12/2024

WARNING: ALL-CAUSE MORTALITY

See full prescribing information for complete boxed warning.

All-cause mortality was higher in patients treated with tigecycline for injection than comparators in a meta-analysis of clinical trials. The cause of this mortality risk difference of 0.6% (95% CI 0.1, 1.2) has not been established. Tigecycline for injection should be reserved for use in situations when alternative treatments are not suitable (1.4, 5.1, 5.2, 6.1).

1 INDICATIONS AND USAGE

Tigecycline is a tetracycline class antibacterial indicated in patients 18 years of age and older for:

- Complicated skin and skin structure infections (1.1)
- Complicated intra-abdominal infections (1.2)
- Community-acquired bacterial pneumonia (1.3)

Limitations of Use: Tigecycline for injection is not indicated for treatment of diabetic foot infection or hospital-acquired pneumonia, including ventilator-associated pneumonia. (1.4)

To reduce the development of drug-resistant bacteria and maintain the effectiveness of tigecycline for injection and other antibacterial drugs, tigecycline for injection should be used only to treat infections that are proven or strongly suspected to be caused by bacteria. (1.5)

2 DOSAGE AND ADMINISTRATION

- Initial dose of 100 mg, followed by 50 mg every 12 hours administered by intravenous infusion over approximately 30 minutes to 60 minutes. (2.1)
- Severe hepatic impairment (Child Pugh C): Initial dose of 100 mg followed by 25 mg every 12 hours. (2.2)
- Obtain baseline blood coagulation parameters, including fibrinogen, and continue to monitor regularly during treatment with tigecycline for injection. (2.4, 5.6)
- See Full Prescribing Information for instructions on reconstitution of the lyophilized powder, and preparation and administration of the intravenous infusion. (2.4)

3 DOSAGE FORMS AND STRENGTHS

For Injection: 50 mg, lyophilized powder for reconstitution in a single-dose vial. (3)

4 CONTRAINDICATIONS

Known hypersensitivity to tigecycline. (4)

5 WARNINGS AND PRECAUTIONS

- All-Cause Mortality: A meta-analysis of Phase 3 and 4 clinical trials demonstrated an increase in all-cause mortality in tigecycline-treated patients compared to controls with a risk difference of 0.6% (95% CI 0.1, 1.2). The cause of this increase has not been established. An increase was also seen in a meta-analysis limited to the approved indications [0.6% (95% CI 0.0, 1.2)]. The greatest difference in mortality was seen in tigecycline-treated patients with ventilator-associated pneumonia. (5.1, 5.2)
- Anaphylactic Reactions: have been reported with tigecycline, and may be life-threatening. Avoid use in patients with known hypersensitivity to tetracyclines. (5.3)
- Hepatic Adverse Effects: have been reported with tigecycline. Patients who develop abnormal liver function tests during tigecycline therapy should be monitored for evidence of worsening hepatic function and evaluated for risk/benefit of continuing tigecycline therapy. (5.4)
- Pancreatitis: including fatalities, has been reported with tigecycline. If pancreatitis is suspected, then consider stopping tigecycline. (5.5)
- Monitoring of Blood Coagulation Parameters: Hypofibrinogenemia has been reported with tigecycline for injection. Monitor blood coagulation parameters, including fibrinogen, at baseline and regularly during treatment with tigecycline for injection. (5.6)
- Tooth Discoloration and Enamel Hypoplasia: The use of tigecycline for injection during tooth development (last half of pregnancy, infancy, and childhood to the age of 8 years) may cause permanent discoloration of the teeth (yellow-gray-brown) and enamel hypoplasia. (5.7)
- Inhibition of Bone Growth: The use of tigecycline for injection during the second and third trimester of pregnancy, infancy, and childhood up to the age of 8 years may cause reversible inhibition of bone growth. (5.8)
- Clostridioides difficile-Associated Diarrhea (CDAD): evaluate if diarrhea occurs. (5.9)

6 ADVERSE REACTIONS

The most common adverse reactions (incidence >5%) are nausea, vomiting, diarrhea, abdominal pain, headache, and increased serum glutamic pyruvic transaminase (SGPT). (6.1)

To report SUSPECTED ADVERSE REACTIONS, contact Amneal Pharmaceuticals at 1-877-835-5472 or FDA at 1-800-FDA-1088 or www.fda.gov/medwatch.

7 DRUG INTERACTIONS

- Warfarin: Suitable anticoagulation test should be monitored if tigecycline for injection is administered to patients receiving warfarin. (7.1)
- Calcineurin Inhibitors: Serum concentrations of calcineurin inhibitors (e.g., tacrolimus, cyclosporine) should be monitored during treatment with tigecycline for injection due to risk of toxicity. (7.2)

8 USE IN SPECIFIC POPULATIONS

- Lactation: Avoid breastfeeding for longer than 3 weeks while taking tigecycline for injection. A lactating woman may pump and discard breast milk during treatment and for 9 days after the last dose of tigecycline. (8.2)
- Pediatrics: Use in patients under 18 years of age is not recommended. Pediatric trials were not conducted because of the higher risk of mortality seen in adult trials (8.4)

FULL PRESCRIBING INFORMATION

WARNING: ALL-CAUSE MORTALITY

An increase in all-cause mortality has been observed in a meta-analysis of Phase 3 and 4 clinical trials in tigecycline for injection-treated patients versus comparator. The cause of this mortality risk difference of 0.6% (95% CI 0.1, 1.2) has not been established. Tigecycline for injection should be reserved for use in situations when alternative treatments are not suitable [see Indications and Usage (1.4), Warnings and Precautions (5.1, 5.2) and Adverse Reactions (6.1)].

1 INDICATIONS AND USAGE

1.1 Complicated Skin and Skin Structure Infections

Tigecycline for injection is indicated in patients 18 years of age and older for the treatment of complicated skin and skin structure infections caused by susceptible isolates of Escherichia coli, Enterococcus faecalis (vancomycin-susceptible isolates), Staphylococcus aureus (methicillin-susceptible and -resistant isolates), Streptococcus agalactiae, Streptococcus anginosus grp. (includes S. anginosus, S. intermedius, and S. constellatus), Streptococcus pyogenes, Enterobacter cloacae, Klebsiella pneumoniae, and Bacteroides fragilis.

1.2 Complicated Intra-abdominal Infections

Tigecycline for injection is indicated in patients 18 years of age and older for the treatment of complicated intra-abdominal infections caused by susceptible isolates of Citrobacter freundii, Enterobacter cloacae, Escherichia coli, Klebsiella oxytoca, Klebsiella pneumoniae, Enterococcus faecalis (vancomycin-susceptible isolates), Staphylococcus aureus (methicillin-susceptible and -resistant isolates), Streptococcus anginosus grp. (includes S. anginosus, S. intermedius, and S. constellatus), Bacteroides fragilis, Bacteroides thetaiotaomicron, Bacteroides uniformis, Bacteroides vulgatus, Clostridium perfringens, and Peptostreptococcus micros.

1.3 Community-Acquired Bacterial Pneumonia

Tigecycline for injection is indicated in patients 18 years of age and older for the treatment of community-acquired bacterial pneumonia caused by susceptible isolates of Streptococcus pneumoniae (penicillin-susceptible isolates), including cases with concurrent bacteremia, Haemophilus influenzae, and Legionella pneumophila.

1.4 Limitations of Use

Tigecycline for injection is not indicated for the treatment of diabetic foot infections. A clinical trial failed to demonstrate non-inferiority of tigecycline for treatment of diabetic foot infections.

Tigecycline for injection is not indicated for the treatment of hospital-acquired or ventilator-associated pneumonia. In a comparative clinical trial, greater mortality and decreased efficacy were reported in tigecycline-treated patients [see Warnings and Precautions (5.2)].

1.5 Usage

To reduce the development of drug-resistant bacteria and maintain the effectiveness of tigecycline for injection and other antibacterial drugs, tigecycline for injection should be used only to treat infections that are proven or strongly suspected to be caused by susceptible bacteria. When culture and susceptibility information are available, they should be considered in selecting or modifying antibacterial therapy. In the absence of such data, local epidemiology and susceptibility patterns may contribute to the empiric selection of therapy.

Appropriate specimens for bacteriological examination should be obtained in order to isolate and identify the causative organisms and to determine their susceptibility to tigecycline. Tigecycline for injection may be initiated as empiric monotherapy before results of these tests are known.

2 DOSAGE AND ADMINISTRATION

2.1 Recommended Adult Dosage

The recommended dosage regimen for tigecycline for injection is an initial dose of 100 mg, followed by 50 mg every 12 hours. Intravenous infusions of tigecycline for injection should be administered over approximately 30 minutes to 60 minutes every 12 hours.

The recommended duration of treatment with tigecycline for injection for complicated skin and skin structure infections or for complicated intra-abdominal infections is 5 days to 14 days. The recommended duration of treatment with tigecycline for injection for community-acquired bacterial pneumonia is 7 days to 14 days. The duration of therapy should be guided by the severity and site of the infection and the patient’s clinical and bacteriological progress.

2.2 Dosage in Patients With Hepatic Impairment

No dosage adjustment is warranted in patients with mild to moderate hepatic impairment (Child Pugh A and Child Pugh B). In patients with severe hepatic impairment (Child Pugh C), the initial dose of tigecycline for injection should be 100 mg followed by a reduced maintenance dose of 25 mg every 12 hours. Patients with severe hepatic impairment (Child Pugh C) should be treated with caution and monitored for treatment response [see Clinical Pharmacology (12.3) and Use in Specific Populations (8.6)].

2.3 Dosage in Pediatric Patients

The safety and efficacy of the proposed pediatric dosing regimens have not been evaluated due to the observed increase in mortality associated with tigecycline for injection in adult patients. Avoid use of tigecycline for injection in pediatric patients unless no alternative antibacterial drugs are available. Under these circumstances, the following doses are suggested:

- Pediatric patients aged 8 years to 11 years should receive 1.2 mg/kg of tigecycline for injection every 12 hours by intravenous infusion over approximately 30 minutes to 60 minutes to a maximum dose of 50 mg of tigecycline for injection every 12 hours.
- Pediatric patients aged 12 years to 17 years should receive 50 mg of tigecycline for injection every 12 hours by intravenous infusion over approximately 30 minutes to 60 minutes.

The proposed pediatric doses of tigecycline for injection were chosen based on exposures observed in pharmacokinetic trials, which included small numbers of pediatric patients [see Use in Specific Populations (8.4) and Clinical Pharmacology (12.3)].

There are no data to provide dosing recommendations in pediatric patients with hepatic impairment.

2.4 Monitoring of Blood Coagulation Parameters

Obtain baseline blood coagulation parameters, including fibrinogen, and continue to monitor regularly during treatment with tigecycline [see Warnings and Precautions (5.6)].

2.5 Preparation and Administration

Reconstitution and Dilution:

Each vial of tigecycline for injection should be reconstituted with 5.3 mL of 0.9% Sodium Chloride Injection, USP, 5% Dextrose Injection, USP, or Lactated Ringer’s Injection, USP to achieve a concentration of 10 mg/mL of tigecycline. (Note: Each vial contains a 6% overage. Thus, 5 mL of reconstituted solution is equivalent to 50 mg of the drug.) The vial should be gently swirled until the drug dissolves. Reconstituted solution must be transferred and further diluted for intravenous infusion. Withdraw 5 mL of the reconstituted solution from the vial and add to a 100 mL intravenous bag for infusion (for a 100 mg dose, reconstitute two vials; for a 50 mg dose, reconstitute one vial). The maximum concentration in the intravenous bag should be 1 mg/mL. The reconstituted solution should be yellow to orange in color; if not, the solution should be discarded. Parenteral drug products should be inspected visually for particulate matter and discoloration (e.g., green or black) prior to administration.

Storage of Reconstituted Solution

Once reconstituted, tigecycline for injection may be stored at room temperature (not to exceed 25°C/77°F) for up to 24 hours (up to 6 hours in the vial and the remaining time in the intravenous bag). If the storage conditions exceed 25°C (77°F) after reconstitution, tigecycline should be used immediately. Alternatively, tigecycline for injection mixed with 0.9% Sodium Chloride Injection, USP or 5% Dextrose Injection, USP may be stored refrigerated at 2°C to 8°C (36°F to 46°F) for up to 48 hours following immediate transfer of the reconstituted solution into the intravenous bag.

Administration of the Diluted Solution

Tigecycline for injection may be administered by intravenous infusion through a dedicated line or through a Y-site. If the same intravenous line is used for sequential infusion of several drugs, the line should be flushed before and after infusion of tigecycline for injection with 0.9% Sodium Chloride Injection, USP, 5% Dextrose Injection, USP or Lactated Ringer’s Injection, USP. Injection should be made with an infusion solution compatible with tigecycline and with any other drug(s) administered via this common line.

2.6 Drug Compatibilities

Compatible intravenous solutions include 0.9% Sodium Chloride Injection, USP, 5% Dextrose Injection, USP, and Lactated Ringer’s Injection, USP. When administered through a Y-site, tigecycline for injection is compatible with the following drugs or diluents when used with either 0.9% Sodium Chloride Injection, USP or 5% Dextrose Injection, USP: amikacin, dobutamine, dopamine HCl, gentamicin, haloperidol, Lactated Ringer’s, lidocaine HCl, metoclopramide, morphine, norepinephrine, piperacillin/tazobactam (EDTA formulation), potassium chloride, propofol, ranitidine HCl, theophylline, and tobramycin.

2.7 Drug Incompatibilities

The following drugs should not be administered simultaneously through the same Y-site as tigecycline for injection: amphotericin B, amphotericin B lipid complex, diazepam, esomeprazole and omeprazole.

3 DOSAGE FORMS AND STRENGTHS

For Injection: Each single-dose glass vial contains 50 mg of tigecycline, USP as an orange lyophilized powder for reconstitution.

4 CONTRAINDICATIONS

Tigecycline for injection is contraindicated for use in patients who have known hypersensitivity to tigecycline. Reactions have included anaphylactic reactions [see Warnings and Precautions (5.3) and Adverse Reactions (6.2)].

5 WARNINGS AND PRECAUTIONS

5.1 All-Cause Mortality

An increase in all-cause mortality has been observed in a meta-analysis of Phase 3 and 4 clinical trials in tigecycline-treated patients versus comparator-treated patients. In all 13 Phase 3 and 4 trials that included a comparator, death occurred in 4.0% (150/3788) of patients receiving tigecycline and 3.0% (110/3646) of patients receiving comparator drugs. In a pooled analysis of these trials, based on a random effects model by trial weight, the adjusted risk difference of all-cause mortality was 0.6% (95% CI 0.1, 1.2) between tigecycline and comparator-treated patients. An analysis of mortality in all trials conducted for approved indications (cSSSI, cIAI, and CABP), including post-market trials showed an adjusted mortality rate of 2.5% (66/2640) for tigecycline and 1.8% (48/2628) for comparator, respectively. The adjusted risk difference for mortality stratified by trial weight was 0.6% (95% CI 0.0, 1.2).

The cause of this mortality difference has not been established. Generally, deaths were the result of worsening infection, complications of infection or underlying co-morbidities. Tigecycline for injection should be reserved for use in situations when alternative treatments are not suitable [see Boxed Warning, Indications and Usage (1.4), Warnings and Precautions (5.2) and Adverse Reactions (6.1)].

5.2 Mortality Imbalance and Lower Cure Rates in Hospital-Acquired Pneumonia

A trial of patients with hospital acquired, including ventilator-associated, pneumonia failed to demonstrate the efficacy of tigecycline. In this trial, patients were randomized to receive tigecycline (100 mg initially, then 50 mg every 12 hours) or a comparator. In addition, patients were allowed to receive specified adjunctive therapies. The sub-group of patients with ventilator-associated pneumonia who received tigecycline had lower cure rates (47.9% versus 70.1% for the clinically evaluable population).

In this trial, greater mortality was seen in patients with ventilator-associated pneumonia who received tigecycline (25/131 [19.1%] versus 15/122 [12.3%] in comparator-treated patients) [see Adverse Reactions (6.1)]. Particularly high mortality was seen among tigecycline-treated patients with ventilator-associated pneumonia and bacteremia at baseline (9/18 [50.0%] versus 1/13 [7.7%] in comparator-treated patients).

5.3 Anaphylactic Reactions

Anaphylactic reactions have been reported with nearly all antibacterial agents, including tigecycline, and may be life-threatening. Tigecycline is structurally similar to tetracycline-class antibacterial drugs and should be avoided in patients with known hypersensitivity to tetracycline-class antibacterial drugs.

5.4 Hepatic Adverse Effects

Increases in total bilirubin concentration, prothrombin time and transaminases have been seen in patients treated with tigecycline. Isolated cases of significant hepatic dysfunction and hepatic failure have been reported in patients being treated with tigecycline. Some of these patients were receiving multiple concomitant medications. Patients who develop abnormal liver function tests during tigecycline therapy should be monitored for evidence of worsening hepatic function and evaluated for risk/benefit of continuing tigecycline for injection therapy. Hepatic dysfunction may occur after the drug has been discontinued.

5.5 Pancreatitis

Acute pancreatitis, including fatal cases, has occurred in association with tigecycline treatment. The diagnosis of acute pancreatitis should be considered in patients taking tigecycline for injection who develop clinical symptoms, signs, or laboratory abnormalities suggestive of acute pancreatitis. Cases have been reported in patients without known risk factors for pancreatitis. Patients usually improve after tigecycline discontinuation. Consideration should be given to the cessation of the treatment with tigecycline for injection in cases suspected of having developed pancreatitis [see Adverse Reactions (6.2)].

5.6 Monitoring of Blood Coagulation Parameters

Hypofibrinogenemia has been reported in patients treated with tigecycline [see Adverse Reactions (6.2)]. Obtain baseline blood coagulation parameters, including fibrinogen, and continue to monitor regularly during treatment with tigecycline.

5.7 Tooth Discoloration and Enamel Hypoplasia

The use of tigecycline for injection during tooth development (last half of pregnancy, infancy, and childhood to the age of 8 years) may cause permanent discoloration of the teeth (yellow-gray-brown). This adverse reaction is more common during long-term use of tetracyclines, but it has been observed following repeated short-term courses. Enamel hypoplasia has also been reported. Advise the patient of the potential risk to the fetus if tigecycline for injection is used during the second or third trimester of pregnancy [see Use in Specific Populations (8.1, 8.4)].

5.8 Inhibition of Bone Growth

The use of tigecycline for injection during the second and third trimester of pregnancy, infancy and childhood up to the age of 8 years may cause reversible inhibition of bone growth. All tetracyclines form a stable calcium complex in any bone-forming tissue. A decrease in fibula growth rate has been observed in premature infants given oral tetracycline in doses of 25 mg/kg every 6 hours. This reaction was shown to be reversible when the tetracycline was discontinued. Advise the patient of the potential risk to the fetus if tigecycline for injection is used during the second or third trimester of pregnancy [see Use in Specific Populations (8.1, 8.4)].

5.9 Clostridioides difficile-Associated Diarrhea

Clostridioides difficile-associated diarrhea (CDAD) has been reported with use of nearly all antibacterial agents, including tigecycline, and may range in severity from mild diarrhea to fatal colitis. Treatment with antibacterial agents alters the normal flora of the colon leading to overgrowth of C. difficile.

C. difficile produces toxins A and B which contribute to the development of CDAD. Hypertoxin producing strains of C. difficile cause increased morbidity and mortality, as these infections can be refractory to antimicrobial therapy and may require colectomy. CDAD must be considered in all patients who present with diarrhea following antibacterial drug use. Careful medical history is necessary since CDAD has been reported to occur over two months after the administration of antibacterial agents.

If CDAD is suspected or confirmed, ongoing antibacterial drug use not directed against C. difficile may need to be discontinued. Appropriate fluid and electrolyte management, protein supplementation, antibacterial drug treatment of C. difficile, and surgical evaluation should be instituted as clinically indicated.

5.10 Sepsis/Septic Shock in Patients With Intestinal Perforation

Monotherapy with tigecycline for injection should be avoided in patients with complicated intra-abdominal infections (cIAI) secondary to clinically apparent intestinal perforation. In cIAI studies (n=1642), 6 patients treated with tigecycline and 2 patients treated with imipenem/cilastatin presented with intestinal perforations and developed sepsis/septic shock. The 6 patients treated with tigecycline had higher APACHE II scores (median = 13) versus the 2 patients treated with imipenem/cilastatin (APACHE II scores = 4 and 6). Due to differences in baseline APACHE II scores between treatment groups and small overall numbers, the relationship of this outcome to treatment cannot be established.

5.11 Tetracycline-Class Adverse Effects

Tigecycline for injection is structurally similar to tetracycline-class antibacterial drugs and may have similar adverse effects. Such effects may include: photosensitivity, fixed drug eruption, pseudotumor cerebri, and anti-anabolic action (which has led to increased BUN, azotemia, acidosis, and hyperphosphatemia). Discontinue tigecycline for injection if any of these adverse reactions are suspected.

5.12 Development of Drug-Resistant Bacteria

Prescribing tigecycline for injection in the absence of a proven or strongly suspected bacterial infection is unlikely to provide benefit to the patient and increases the risk of the development of drug-resistant bacteria.

6 ADVERSE REACTIONS

The following serious adverse reactions are described elsewhere in the labeling:

- All-Cause Mortality [see Boxed Warning and Warnings and Precautions (5.1)]
- Mortality Imbalance and Lower Cure Rates in Hospital-Acquired Pneumonia [see Warnings and Precautions (5.2)]
- Anaphylaxis [see Warning and Precautions (5.3)]
- Hepatic Adverse Effects [see Warnings and Precautions (5.4)]
- Pancreatitis [see Warnings and Precautions (5.5)]

6.1 Clinical Trials Experience

Because clinical trials are conducted under widely varying conditions, adverse reaction rates observed in the clinical trials of a drug cannot be directly compared to rates in the clinical trials of another drug and may not reflect the rates observed in practice.

In clinical trials, 2,514 patients were treated with tigecycline for injection. Tigecycline for injection was discontinued due to adverse reactions in 7% of patients compared to 6% for all comparators. Table 1 shows the incidence of adverse reactions through test of cure reported in ≥2% of patients in these trials.

Table 1. Incidence (%) of Adverse Reactions Through Test of Cure Reported in ≥ 2% of Patients Treated in Clinical Studies

Body System; Adverse Reactions | Tigecycline for Injection (N=2514) |  | Comparatorsa (N=2307)
Body as a Whole
Abdominal pain | 6 |  | 4
Abscess | 2 |  | 2
Asthenia | 3 |  | 2
Headache | 6 |  | 7
Infection | 7 |  | 5
Cardiovascular System
Phlebitis | 3 |  | 4
Digestive System
Diarrhea | 12 |  | 11
Dyspepsia | 2 |  | 2
Nausea | 26 |  | 13
Vomiting | 18 |  | 9
Hemic and Lymphatic System
Anemia |  | 5 | 6
Metabolic and Nutritional
Alkaline Phosphatase Increased |  | 3 | 3
Amylase Increased |  | 3 | 2
Bilirubinemia |  | 2 | 1
BUN Increased |  | 3 | 1
Healing Abnormal |  | 3 | 2
Hyponatremia |  | 2 | 1
Hypoproteinemia |  | 5 | 3
SGOT Increasedb |  | 4 | 5
SGPT Increasedb |  | 5 | 5
Respiratory System
Pneumonia |  | 2 | 2
Nervous System
Dizziness |  | 3 | 3
Skin and Appendages
Rash |  | 3 | 4
a Vancomycin/Aztreonam, Imipenem/Cilastatin, Levofloxacin, Linezolid.
b LFT abnormalities in tigecycline-treated patients were reported more frequently in the post therapy period than those in comparator-treated patients, which occurred more often on therapy.

In all 13 Phase 3 and 4 trials that included a comparator, death occurred in 4.0% (150/3788) of patients receiving tigecycline for injection and 3.0% (110/3646) of patients receiving comparator drugs. In a pooled analysis of these trials, based on a random effects model by trial weight, an adjusted risk difference of all-cause mortality was 0.6% (95% CI 0.1, 1.2) between tigecycline for injection and comparator-treated patients (see Table 2). The cause of the imbalance has not been established. Generally, deaths were the result of worsening infection, complications of infection or underlying co-morbidities.

Table 2. Patients with Outcome of Death by Infection Type

 | Tigecycline for Injection |  | Comparator |  | Risk Difference*
Infection Type | n/N | % | n/N | % | % (95% CI)
cSSSI | 12/834 | 1.4 | 6/813 | 0.7 | 0.7 (-0.3, 1.7)
cIAI | 42/1382 | 3.0 | 31/1393 | 2.2 | 0.8 (-0.4, 2.0)
CAP | 12/424 | 2.8 | 11/422 | 2.6 | 0.2 (-2.0, 2.4)
HAP | 66/467 | 14.1 | 57/467 | 12.2 | 1.9 (-2.4, 6.3)
Non-VAPa | 41/336 | 12.2 | 42/345 | 12.2 | 0.0 (-4.9, 4.9)
VAPa | 25/131 | 19.1 | 15/122 | 12.3 | 6.8 (-2.1, 15.7)
RP | 11/128 | 8.6 | 2/43 | 4.7 | 3.9 (-4.0, 11.9)
DFI | 7/553 | 1.3 | 3/508 | 0.6 | 0.7 (-0.5, 1.8)
Overall Adjusted | 150/3788 | 4.0 | 110/3646 | 3.0 | 0.6 (0.1, 1.2)**
CAP = Community-acquired pneumonia; cIAI = Complicated intra-abdominal infections;
cSSSI = Complicated skin and skin structure infections; HAP = Hospital-acquired pneumonia;
VAP = Ventilator-associated pneumonia; RP = Resistant pathogens; DFI = Diabetic foot infections.
* The difference between the percentage of patients who died in tigecycline and comparator treatment groups. The 95% CI for each infection type was calculated using the normal approximation method without continuity correction.
** Overall adjusted (random effects model by trial weight) risk difference estimate and 95% CI.
a These are subgroups of the HAP population.
Note: The studies include 300, 305, 900 (cSSSI), 301, 306, 315, 316, 400 (cIAI), 308 and 313 (CAP), 311 (HAP), 307 [Resistant gram-positive pathogen study in patients with MRSA or Vancomycin-Resistant Enterococcus (VRE)], and 319 (DFI with and without osteomyelitis).

An analysis of mortality in all trials conducted for approved indications - cSSSI, cIAI, and CABP, including post-market trials (one in cSSSI and two in cIAI) - showed an adjusted mortality rate of 2.5% (66/2640) for tigecycline and 1.8% (48/2628) for comparator, respectively. The adjusted risk difference for mortality stratified by trial weight was 0.6% (95% CI 0.0, 1.2).

In comparative clinical studies, infection-related serious adverse reactions were more frequently reported for subjects treated with tigecycline for injection (7%) versus comparators (6%). Serious adverse reactions of sepsis/septic shock were more frequently reported for subjects treated with tigecycline for injection (2%) versus comparators (1%). Due to baseline differences between treatment groups in this subset of patients, the relationship of this outcome to treatment cannot be established [see Warnings and Precautions (5.10)].

The most common adverse reactions were nausea and vomiting which generally occurred during the first 1 – 2 days of therapy. The majority of cases of nausea and vomiting associated with tigecycline for injection and comparators were either mild or moderate in severity. In patients treated with tigecycline for injection, nausea incidence was 26% (17% mild, 8% moderate, 1% severe) and vomiting incidence was 18% (11% mild, 6% moderate, 1% severe).

In patients treated for complicated skin and skin structure infections (cSSSI), nausea incidence was 35% for tigecycline for injection and 9% for vancomycin/aztreonam; vomiting incidence was 20% for tigecycline for injection and 4% for vancomycin/aztreonam. In patients treated for complicated intra-abdominal infections (cIAI), nausea incidence was 25% for tigecycline for injection and 21% for imipenem/cilastatin; vomiting incidence was 20% for tigecycline for injection and 15% for imipenem/cilastatin. In patients treated for community-acquired bacterial pneumonia (CABP), nausea incidence was 24% for tigecycline for injection and 8% for levofloxacin; vomiting incidence was 16% for tigecycline and 6% for levofloxacin.

Discontinuation from tigecycline for injection was most frequently associated with nausea (1%) and vomiting (1%). For comparators, discontinuation was most frequently associated with nausea (<1%).

The following adverse reactions were reported (<2%) in patients receiving tigecycline for injection in clinical studies:

Body as a Whole: injection site inflammation, injection site pain, injection site reaction, septic shock, allergic reaction, chills, injection site edema, injection site phlebitis

Cardiovascular System: thrombophlebitis

Digestive System: anorexia, jaundice, abnormal stools

Metabolic/Nutritional System: increased creatinine, hypocalcemia, hypoglycemia

Special Senses: taste perversion

Hemic and Lymphatic System: prolonged activated partial thromboplastin time (aPTT), prolonged prothrombin time (PT), eosinophilia, increased international normalized ratio (INR), thrombocytopenia

Skin and Appendages: pruritus

Urogenital System: vaginal moniliasis, vaginitis, leukorrhea

6.2 Post-Marketing Experience

The following adverse reactions have been identified during post-approval use of tigecycline for injection. Because these reactions are reported voluntarily from a population of uncertain size, it is not always possible to reliably estimate their frequency or establish causal relationship to drug exposure.

- anaphylactic reactions
- acute pancreatitis
- hepatic cholestasis, and jaundice
- severe skin reactions, including Stevens-Johnson Syndrome
- symptomatic hypoglycemia in patients with and without diabetes mellitus
- hypofibrinogenemia [see Warnings and Precautions (5.6)]

7 DRUG INTERACTIONS

7.1 Warfarin

Prothrombin time or other suitable anticoagulation test should be monitored if tigecycline for injection is administered with warfarin [see Clinical Pharmacology (12.3)].

7.2 Calcineurin Inhibitors

Concomitant use of tigecycline for injection and calcineurin inhibitors such as tacrolimus or cyclosporine may lead to an increase in serum trough concentrations of the calcineurin inhibitors. Therefore, serum concentrations of the calcineurin inhibitor should be monitored during treatment with tigecycline for injection to avoid drug toxicity.

7.3 Oral Contraceptives

Concurrent use of antibacterial drugs with oral contraceptives may render oral contraceptives less effective.

8 USE IN SPECIFIC POPULATIONS

8.1 Pregnancy

Risk Summary

Tigecycline for injection, like other tetracycline class antibacterial drugs, may cause permanent discoloration of deciduous teeth and reversible inhibition of bone growth when administered during the second and third trimesters of pregnancy [see Warnings and Precautions (5.7), (5.8), Data, and Use in Specific Populations (8.4)]. There are no available data on the risk of major birth defects or miscarriage following the use of tigecycline for injection during pregnancy. Administration of intravenous tigecycline in pregnant rats and rabbits during the period of organogenesis was associated with reduction in fetal weights and an increased incidence of skeletal anomalies (delays in bone ossification) at exposures of 5 and 1 times the human exposure at the recommended clinical dose in rats and rabbits, respectively. Advise the patient of the potential risk to the fetus if tigecycline for injection is used during the second or third trimester.

The estimated background risk of major birth defects and miscarriage for the indicated population is unknown. All pregnancies have a background risk of birth defect, loss, or other adverse outcomes. In the U. S. general population, the estimated background risk in clinically recognized pregnancies is 2% to 4% and 15% to 20%, respectively.

Data

Human Data

The use of tetracycline-class antibacterial drugs, that includes tigecycline for injection, during tooth development (second and third trimester of pregnancy) may cause permanent discoloration of deciduous teeth. This adverse reaction is more common during long-term use of tetracyclines but has been observed following repeated short-term courses. Tigecycline for injection may cause reversible inhibition of bone growth when administered during the second and third trimesters of pregnancy. A decrease in fibula growth rate has been observed in premature infants given oral tetracycline in doses of 25 mg/kg every 6 hours.

Animal Data

In embryo-fetal development studies, tigecycline was administered during the period of organogenesis at doses up to 12 mg/kg/day in rats and 4 mg/kg in rabbits or 5 and 1 times the systemic exposure at the recommended clinical dose, respectively. In the rat study, decreased fetal weight and fetal skeletal variations (reduced ossification of the pubic, ischial, and supraoccipital bones and increased incidences of rudimentary 14th rib) were observed in the presence of maternal toxicity at 12 mg/kg/day (5 times the recommended clinical dose based on systemic exposure). In rabbits, decreased fetal weights were observed in the presence of maternal toxicity at 4 mg/kg (equivalent to the human exposure at the recommended clinical dose).

In preclinical safety studies, ^14C-labeled tigecycline crossed the placenta and was found in fetal tissues.

8.2 Lactation

Risk Summary

There are no data on the presence of tigecycline in human milk; however, tetracycline-class antibacterial drugs are present in breast milk. It is not known whether tigecycline has an effect on the breastfed infant or on milk production. Tigecycline has low oral bioavailability; therefore, infant exposure is expected to be low. Tigecycline is present in rat milk with little or no systemic exposure to tigecycline in nursing pups as a result of exposure via maternal milk. When a drug is present in animal milk, it is likely that the drug will be present in human milk.

The developmental and health benefits of breastfeeding should be considered along with the mother’s clinical need for tigecycline for injection and any potential adverse effects on the breastfed child from tigecycline for injection or from the underlying maternal condition (see Clinical Considerations).

Clinical Considerations

Because of the theoretical risk of dental discoloration and inhibition of bone growth, avoid breastfeeding if taking tigecycline for injection for longer than three weeks. A lactating woman may also consider interrupting breastfeeding and pumping and discarding breastmilk during administration of tigecycline for injection and for 9 days (approximately 5 half-lives) after the last dose in order to minimize drug exposure to a breastfed infant.

8.4 Pediatric Use

Use in patients under 18 years of age is not recommended. Safety and effectiveness in pediatric patients below the age of 18 years have not been established. Because of the increased mortality observed in tigecycline for injection-treated adult patients in clinical trials, pediatric trials of tigecycline for injection to evaluate the safety and efficacy of tigecycline were not conducted.

In situations where there are no other alternative antibacterial drugs, dosing has been proposed for pediatric patients 8 to 17 years of age based on data from pediatric pharmacokinetic studies [see Dosage and Administration (2.3) and Clinical Pharmacology (12.3)].

Because of effects on tooth development, use in patients under 8 years of age is not recommended [see Warnings and Precautions (5.7)].

8.5 Geriatric Use

Of the total number of subjects who received tigecycline in Phase 3 clinical studies (n=2514), 664 were 65 and over, while 288 were 75 and over. No overall differences in safety or effectiveness were observed between these subjects and younger subjects, but greater sensitivity to adverse events of some older individuals cannot be ruled out.

No significant difference in tigecycline exposure was observed between healthy elderly subjects and younger subjects following a single 100 mg dose of tigecycline [see Clinical Pharmacology (12.3)].

8.6 Hepatic Impairment

No dosage adjustment is warranted in patients with mild to moderate hepatic impairment (Child Pugh A and Child Pugh B). In patients with severe hepatic impairment (Child Pugh C), the initial dose of tigecycline should be 100 mg followed by a reduced maintenance dose of 25 mg every 12 hours. Patients with severe hepatic impairment (Child Pugh C) should be treated with caution and monitored for treatment response [see Clinical Pharmacology (12.3) and Dosage and Administration (2.2)].

10 OVERDOSAGE

No specific information is available on the treatment of overdosage with tigecycline. Intravenous administration of tigecycline for injection at a single dose of 300 mg over 60 minutes in healthy volunteers resulted in an increased incidence of nausea and vomiting. Tigecycline is not removed in significant quantities by hemodialysis.

11 DESCRIPTION

Tigecycline for injection, USP is a tetracycline class antibacterial for intravenous infusion. The chemical name of tigecycline, USP is (4S,4aS,5aR,12aS)-9-[2-(tert-butylamino)acetamido]-4,7-bis(dimethylamino)-1,4,4a,5,5a,6,11,12a-octahydro-3,10,12,12a-tetrahydroxy-1,11-dioxo-2-naphthacenecarboxamide. The empirical formula is C29H39N5O8 and the molecular weight is 585.65.

The following represents the chemical structure of tigecycline, USP:

Figure 1: Structure of Tigecycline

Tigecycline, USP is an orange lyophilized sterile powder or cake. Each tigecycline for injection, USP single-dose 5 mL vial contains 50 mg tigecycline, USP lyophilized powder for reconstitution for intravenous infusion and 50 mg of L-Arginine. The pH is adjusted with hydrochloric acid, and if necessary sodium hydroxide. The product does not contain preservatives.

12 CLINICAL PHARMACOLOGY

12.1 Mechanism of Action

Tigecycline is a tetracycline class antibacterial drug [see Microbiology (12.4)].

12.2 Pharmacodynamics

Cardiac Electrophysiology

No significant effect of a single intravenous dose of tigecycline 50 mg or 200 mg on QTc interval was detected in a randomized, placebo- and active-controlled four-arm crossover thorough QTc study of 46 healthy subjects.

12.3 Pharmacokinetics

The mean pharmacokinetic parameters of tigecycline after single and multiple intravenous doses based on pooled data from clinical pharmacology studies are summarized in Table 3. Intravenous infusions of tigecycline were administered over approximately 30 to 60 minutes.

Table 3. Mean (CV%) Pharmacokinetic Parameters of Tigecycline

 | Single Dose | Multiple Dosea
 | 100 mg | 50 mg every 12h
 | (N=224) | (N=103)
Cmax (mcg/mL)b | 1.45 (22%) | 0.87 (27%)
Cmax (mcg/mL)c | 0.90 (30%) | 0.63 (15%)
AUC (mcg·h/mL) | 5.19 (36%) | - -
AUC0-24h (mcg·h/mL) | - - | 4.70 (36%)
Cmin (mcg/mL) | - - | 0.13 (59%)
t1/2 (h) | 27.1 (53%) | 42.4 (83%)
CL (L/h) | 21.8 (40%) | 23.8 (33%)
CLr (mL/min) | 38.0 (82%) | 51.0 (58%)
Vss (L) | 568 (43%) | 639 (48%)
a 100 mg initially, followed by 50 mg every 12 hours
b 30-minute infusion
c 60-minute infusion

Distribution

The in vitro plasma protein binding of tigecycline ranges from approximately 71% to 89% at concentrations observed in clinical studies (0.1 to 1 mcg/mL). The steady-state volume of distribution of tigecycline averaged 500 to 700 L (7 to 9 L/kg), indicating tigecycline is extensively distributed beyond the plasma volume and into the tissues.

Following the administration of tigecycline 100 mg followed by 50 mg every 12 hours to 33 healthy volunteers, the tigecycline AUC0-12h (134 mcg·h/mL) in alveolar cells was approximately 78-fold higher than the AUC0-12h in the serum, and the AUC0-12h (2.28 mcg·h/mL) in epithelial lining fluid was approximately 32% higher than the AUC0-12h in serum. The AUC0-12h (1.61 mcg·h/mL) of tigecycline in skin blister fluid was approximately 26% lower than the AUC0-12h in the serum of 10 healthy subjects.

In a single-dose study, tigecycline 100 mg was administered to subjects prior to undergoing elective surgery or medical procedure for tissue extraction. Concentrations at 4 hours after tigecycline administration were higher in gallbladder (38-fold, n=6), lung (3.7-fold, n=5), and colon (2.3-fold, n=6), and lower in synovial fluid (0.58-fold, n=5), and bone (0.35-fold, n=6) relative to serum. The concentration of tigecycline in these tissues after multiple doses has not been studied.

Elimination

Metabolism

Tigecycline is not extensively metabolized. In vitro studies with tigecycline using human liver microsomes, liver slices, and hepatocytes led to the formation of only trace amounts of metabolites. In healthy male volunteers receiving ^14C-tigecycline, tigecycline was the primary ^14C-labeled material recovered in urine and feces, but a glucuronide, an N-acetyl metabolite, and a tigecycline epimer (each at no more than 10% of the administered dose) were also present.

Tigecycline is a substrate of P-glycoprotein (P-gp) based on an in vitro study using a cell line overexpressing P-gp. The potential contribution of P-gp-mediated transport to the in vivo disposition of tigecycline is not known.

Excretion

The recovery of total radioactivity in feces and urine following administration of ^14C-tigecycline indicates that 59% of the dose is eliminated by biliary/fecal excretion, and 33% is excreted in urine. Approximately 22% of the total dose is excreted as unchanged tigecycline in urine. Overall, the primary route of elimination for tigecycline is biliary excretion of unchanged tigecycline and its metabolites. Glucuronidation and renal excretion of unchanged tigecycline are secondary routes.

Specific Populations

Hepatic Impairment

In a study comparing 10 patients with mild hepatic impairment (Child Pugh A), 10 patients with moderate hepatic impairment (Child Pugh B), and 5 patients with severe hepatic impairment (Child Pugh C) to 23 age and weight matched healthy control subjects, the single-dose pharmacokinetic disposition of tigecycline was not altered in patients with mild hepatic impairment. However, systemic clearance of tigecycline was reduced by 25% and the half-life of tigecycline was prolonged by 23% in patients with moderate hepatic impairment (Child Pugh B). Systemic clearance of tigecycline was reduced by 55%, and the half-life of tigecycline was prolonged by 43% in patients with severe hepatic impairment (Child Pugh C). Dosage adjustment is necessary in patients with severe hepatic impairment (Child Pugh C) [see Use in Specific Populations (8.6) and Dosage and Administration (2.2)].

Renal Impairment

A single dose study compared 6 subjects with severe renal impairment (creatinine clearance <30 mL/min), 4 end stage renal disease (ESRD) patients receiving tigecycline 2 hours before hemodialysis, 4 ESRD patients receiving tigecycline 1 hour after hemodialysis, and 6 healthy control subjects. The pharmacokinetic profile of tigecycline was not significantly altered in any of the renally impaired patient groups, nor was tigecycline removed by hemodialysis. No dosage adjustment of tigecycline for injection is necessary in patients with renal impairment or in patients undergoing hemodialysis.

Geriatric Patients

No significant differences in pharmacokinetics were observed between healthy elderly subjects (n=15, age 65 to 75; n=13, age >75) and younger subjects (n=18) receiving a single 100-mg dose of tigecycline for injection. Therefore, no dosage adjustment is necessary based on age [see Use in Specific Populations (8.5)].

Pediatric Patients

A single-dose safety, tolerability, and pharmacokinetic study of tigecycline in pediatric patients aged 8 to 16 years who recently recovered from infections was conducted. The doses administered were 0.5, 1, or 2 mg/kg. The study showed that for children aged 12 to 16 years (n = 16) a dosage of 50 mg twice daily would likely result in exposures comparable to those observed in adults with the approved dosing regimen. Large variability observed in children aged 8 to 11 years of age (n = 8) required additional study to determine the appropriate dosage.

A subsequent tigecycline dose-finding study was conducted in 8 to 11 year old patients with cIAI, cSSSI, or CABP. The doses of tigecycline studied were 0.75 mg/kg (n = 17), 1 mg/kg (n = 21), and 1.25 mg/kg (n=20). This study showed that for children aged 8 to 11 years, a 1.2 mg/kg dose would likely result in exposures comparable to those observed in adults resulting with the approved dosing regimen [see Dosage and Administration (2.3)].

Gender

In a pooled analysis of 38 women and 298 men participating in clinical pharmacology studies, there was no significant difference in the mean (±SD) tigecycline clearance between women (20.7±6.5 L/h) and men (22.8±8.7 L/h). Therefore, no dosage adjustment is necessary based on gender.

Race

In a pooled analysis of 73 Asian subjects, 53 Black subjects, 15 Hispanic subjects, 190 White subjects, and 3 subjects classified as “other” participating in clinical pharmacology studies, there was no significant difference in the mean (±SD) tigecycline clearance among the Asian subjects (28.8±8.8 L/h), Black subjects (23.0±7.8 L/h), Hispanic subjects (24.3±6.5 L/h), White subjects (22.1±8.9 L/h), and “other” subjects (25.0±4.8 L/h). Therefore, no dosage adjustment is necessary based on race.

Drug Interaction Studies

Digoxin

Tigecycline (100 mg followed by 50 mg every 12 hours) and digoxin (0.5 mg followed by 0.25 mg, orally, every 24 hours) were co-administered to healthy subjects in a drug interaction study. Tigecycline slightly decreased the Cmax of digoxin by 13%, but did not affect the AUC or clearance of digoxin. This small change in Cmax did not affect the steady-state pharmacodynamic effects of digoxin as measured by changes in ECG intervals. In addition, digoxin did not affect the pharmacokinetic profile of tigecycline. Therefore, no dosage adjustment of either drug is necessary when tigecycline for injection is administered with digoxin.

Warfarin

Concomitant administration of tigecycline for injection (100 mg followed by 50 mg every 12 hours) and warfarin (25 mg single-dose) to healthy subjects resulted in a decrease in clearance of R-warfarin and S-warfarin by 40% and 23%, an increase in Cmax by 38% and 43% and an increase in AUC by 68% and 29%, respectively. Tigecycline did not significantly alter the effects of warfarin on INR. In addition, warfarin did not affect the pharmacokinetic profile of tigecycline. However, prothrombin time or other suitable anticoagulation test should be monitored if tigecycline is administered with warfarin.

In vitro studies in human liver microsomes indicate that tigecycline does not inhibit metabolism mediated by any of the following 6 cytochrome P450 (CYP) isoforms: 1A2, 2C8, 2C9, 2C19, 2D6, and 3A4. Therefore, tigecycline for injection is not expected to alter the metabolism of drugs metabolized by these enzymes. In addition, because tigecycline is not extensively metabolized, clearance of tigecycline is not expected to be affected by drugs that inhibit or induce the activity of these CYP450 isoforms.

In vitro studies using Caco-2 cells indicate that tigecycline does not inhibit digoxin flux, suggesting that tigecycline is not a P-glycoprotein (P-gp) inhibitor. This in vitro information is consistent with the lack of effect of tigecycline on digoxin clearance noted in the in vivo drug interaction study described above.

Tigecycline is a substrate of P-gp based on an in vitro study using a cell line overexpressing P-gp. The potential contribution of P-gp-mediated transport to the in vivo disposition of tigecycline is not known. Co-administration of P-gp inhibitors (e.g., ketoconazole or cyclosporine) or P-gp inducers (e.g., rifampicin) could affect the pharmacokinetics of tigecycline.

12.4 Microbiology

Mechanism of Action

Tigecycline inhibits protein translation in bacteria by binding to the 30S ribosomal subunit and blocking entry of amino-acyl tRNA molecules into the A site of the ribosome. This prevents incorporation of amino acid residues into elongating peptide chains. In general, tigecycline is considered bacteriostatic; however, tigecycline for injection has demonstrated bactericidal activity against isolates of S. pneumoniae and L. pneumophila.

Resistance

To date there has been no cross-resistance observed between tigecycline and other antibacterial drugs. Tigecycline is less affected by the two major tetracycline-resistance mechanisms, ribosomal protection and efflux. Additionally, tigecycline is not affected by resistance mechanisms such as beta-lactamases (including extended spectrum beta-lactamases), target-site modifications, macrolide efflux pumps or enzyme target changes (e.g., gyrase/topoisomerases). However, some ESBL-producing isolates may confer resistance to tigecycline via other resistance mechanisms. Tigecycline resistance in some bacteria (e.g., Acinetobacter calcoaceticus-Acinetobacter baumannii complex) is associated with multi-drug resistant (MDR) efflux pumps.

Interaction with Other Antimicrobials

In vitro studies have not demonstrated antagonism between tigecycline and other commonly used antibacterial drugs.

Antimicrobial Activity

Tigecycline has been shown to be active against most isolates of the following microorganisms, both in vitro and in clinical infections [see Indications and Usage (1)].

Gram-positive bacteria

Enterococcus faecalis (vancomycin-susceptible isolates)

Staphylococcus aureus (methicillin-susceptible and -resistant isolates)

Streptococcus agalactiae

Streptococcus anginosus group (includes S. anginosus, S. intermedius, and S. constellatus)

Streptococcus pneumoniae (penicillin-susceptible isolates)

Streptococcus pyogenes

Gram-negative bacteria

Citrobacter freundii

Enterobacter cloacae

Escherichia coli

Haemophilus influenzae

Klebsiella oxytoca

Klebsiella pneumoniae

Legionella pneumophila

Anaerobic bacteria

Bacteroides fragilis

Bacteroides thetaiotaomicron

Bacteroides uniformis

Bacteroides vulgatus

Clostridium perfringens

Peptostreptococcus micros

The following in vitro data are available, but their clinical significance is unknown. At least 90 percent of the following bacteria exhibit an in vitro minimum inhibitory concentration (MIC) less than or equal to the susceptible breakpoint for tigecycline against isolates of similar genus or organism group. However, the efficacy of tigecycline in treating clinical infections caused by these bacteria has not been established in adequate and well-controlled clinical trials.

Gram-positive bacteria

Enterococcus avium

Enterococcus casseliflavus

Enterococcus faecalis (vancomycin-resistant isolates)

Enterococcus faecium (vancomycin-susceptible and -resistant isolates)

Enterococcus gallinarum

Listeria monocytogenes

Staphylococcus epidermidis (methicillin-susceptible and -resistant isolates)

Staphylococcus haemolyticus

Gram-negative bacteria

Acinetobacter baumannii*

Aeromonas hydrophila

Citrobacter koseri

Enterobacter aerogenes

Haemophilus influenzae (ampicillin-resistant)

Haemophilus parainfluenzae

Pasteurella multocida

Serratia marcescens

Stenotrophomonas maltophilia

Anaerobic bacteria

Bacteroides distasonis

Bacteroides ovatus

Peptostreptococcus spp.

Porphyromonas spp.

Prevotella spp.

Other bacteria

Mycobacterium abscessus

Mycobacterium fortuitum

*There have been reports of the development of tigecycline resistance in Acinetobacter infections seen during the course of standard treatment. Such resistance appears to be attributable to an MDR efflux pump mechanism. While monitoring for relapse of infection is important for all infected patients, more frequent monitoring in this case is suggested. If relapse is suspected, blood and other specimens should be obtained and cultured for the presence of bacteria. All bacterial isolates should be identified and tested for susceptibility to tigecycline and other appropriate antimicrobials.

Susceptibility Testing

For specific information regarding susceptibility test interpretive criteria and associated test methods and quality control standards recognized by FDA for this drug, please see: https://www.fda.gov/STIC

13 NONCLINICAL TOXICOLOGY

13.1 Carcinogenesis, Mutagenesis, Impairment of Fertility

Lifetime studies in animals have not been performed to evaluate the carcinogenic potential of tigecycline. No mutagenic or clastogenic potential was found in a battery of tests, including in vitro chromosome aberration assay in Chinese hamster ovary (CHO) cells, in vitro forward mutation assay in CHO cells (HGRPT locus), in vitro forward mutation assays in mouse lymphoma cells, and in vivo mouse micronucleus assay. Tigecycline did not affect mating or fertility in rats at exposures up to 5 times the human daily dose based on AUC (28 mcg·hr/mL at 12 mg/kg/day). In female rats, there were no compound-related effects on ovaries or estrous cycles at exposures up to 5 times the human daily dose based on AUC.

13.2 Animal Toxicology and/or Pharmacology

In two week studies, decreased erythrocytes, reticulocytes, leukocytes, and platelets, in association with bone marrow hypocellularity, have been seen with tigecycline at exposures of 8 times and 10 times the human daily dose based on AUC in rats and dogs, (AUC of approximately 50 and 60 mcg·hr/mL at doses of 30 and 12 mg/kg/day) respectively. These alterations were shown to be reversible after two weeks of dosing.

14 CLINICAL STUDIES

14.1 Complicated Skin and Skin Structure Infections

Tigecycline for injection was evaluated in adults for the treatment of complicated skin and skin structure infections (cSSSI) in two randomized, double-blind, active-controlled, multinational, multicenter studies (Studies 1 and 2). These studies compared tigecycline for injection (100 mg intravenous initial dose followed by 50 mg every 12 hours) with vancomycin (1 g intravenous every 12 hours)/aztreonam (2 g intravenous every 12 hours) for 5 to 14 days. Patients with complicated deep soft tissue infections including wound infections and cellulitis (≥10 cm, requiring surgery/drainage or with complicated underlying disease), major abscesses, infected ulcers, and burns were enrolled in the studies. The primary efficacy endpoint was the clinical response at the test of cure (TOC) visit in the co-primary populations of the clinically evaluable (CE) and clinical modified intent-to-treat (c-mITT) patients. See Table 4. Clinical cure rates at TOC by pathogen in the microbiologically evaluable patients are presented in Table 5.

Table 4. Clinical Cure Rates from Two Studies in Complicated Skin and Skin Structure Infections after 5 to 14 Days of Therapy

 | Tigecycline a; n/N (%) | Vancomycin/Aztreonamb; n/N (%)
Study 1
CE | 165/199 (82.9) | 163/198 (82.3)
c-mITT | 209/277 (75.5) | 200/260 (76.9)
Study 2
CE | 200/223 (89.7) | 201/213 (94.4)
c-mITT | 220/261 (84.3) | 225/259 (86.9)
a 100 mg initially, followed by 50 mg every 12 hours
b Vancomycin (1 g every 12 hours)/Aztreonam (2 g every 12 hours)

Table 5. Clinical Cure Rates By Infecting Pathogen in Microbiologically Evaluable Patients with Complicated Skin and Skin Structure Infectionsa

Pathogen | Tigecycline; n/N (%) | Vancomycin/Aztreonam; n/N (%)
Escherichia coli | 29/36 (80.6) | 26/30 (86.7)
Enterobacter cloacae | 10/12 (83.3) | 15/15 (100)
Enterococcus faecalis (vancomycin-susceptible only) | 15/21 (71.4) | 19/24 (79.2)
Klebsiella pneumoniae | 12/14 (85.7) | 15/16 (93.8)
Methicillin-susceptible; Staphylococcus aureus (MSSA) | 124/137 (90.5) | 113/120 (94.2)
Methicillin-resistant; Staphylococcus aureus (MRSA) | 79/95 (83.2) | 46/57 (80.7)
Streptococcus agalactiae | 8/8 (100) | 11/14 (78.6)
Streptococcus anginosus grp.b | 17/21 (81.0) | 9/10 (90.0)
Streptococcus pyogenes | 31/32 (96.9) | 24/27 (88.9)
Bacteroides fragilis | 7/9 (77.8) | 4/5 (80.0)
a Two cSSSI pivotal studies and two Resistant Pathogen studies
b Includes Streptococcus anginosus, Streptococcus intermedius, and Streptococcus constellatus

14.2 Complicated Intra-abdominal Infections

Tigecycline for injection was evaluated in adults for the treatment of complicated intra-abdominal infections (cIAI) in two randomized, double-blind, active-controlled, multinational, multicenter studies (Studies 1 and 2). These studies compared tigecycline for injection (100 mg intravenous initial dose followed by 50 mg every 12 hours) with imipenem/cilastatin (500 mg intravenous every 6 hours) for 5 to 14 days. Patients with complicated diagnoses including appendicitis, cholecystitis, diverticulitis, gastric/duodenal perforation, intra-abdominal abscess, perforation of intestine, and peritonitis were enrolled in the studies. The primary efficacy endpoint was the clinical response at the TOC visit for the co-primary populations of the microbiologically evaluable (ME) and the microbiologic modified intent-to-treat (m-mITT) patients. See Table 6. Clinical cure rates at TOC by pathogen in the microbiologically evaluable patients are presented in Table 7.

Table 6. Clinical Cure Rates from Two Studies in Complicated Intra-abdominal Infections

after 5 to 14 Days of Therapy

 | Tigecycline for Injectiona; n/N (%) | Imipenem/Cilastatinb; n/N (%)
Study 1
ME | 199/247 (80.6) | 210/255 (82.4)
m-mITT | 227/309 (73.5) | 244/312 (78.2)
Study 2
ME | 242/265 (91.3) | 232/258 (89.9)
m-mITT | 279/322 (86.6) | 270/319 (84.6)
a 100 mg initially, followed by 50 mg every 12 hours
b Imipenem/Cilastatin (500 mg every 6 hours)

Table 7. Clinical Cure Rates By Infecting Pathogen in Microbiologically Evaluable Patients with Complicated Intra-abdominal Infectionsa

Pathogen | Tigecycline for Injection n/N (%) | Imipenem/Cilastatin; n/N (%)
Citrobacter freundii | 12/16 (75.0) | 3/4 (75.0)
Enterobacter cloacae | 15/17 (88.2) | 16/17 (94.1)
Escherichia coli | 284/336 (84.5) | 297/342 (86.8)
Klebsiella oxytoca | 19/20 (95.0) | 17/19 (89.5)
Klebsiella pneumoniae | 42/47 (89.4) | 46/53 (86.8)
Enterococcus faecalis | 29/38 (76.3) | 35/47 (74.5)
Methicillin-susceptible; Staphylococcus aureus (MSSA) | 26/28 (92.9) | 22/24 (91.7)
Methicillin-resistant; Staphylococcus aureus (MRSA) | 16/18 (88.9) | 1/3 (33.3)
Streptococcus anginosus grp.b | 101/119 (84.9) | 60/79 (75.9)
Bacteroides fragilis | 68/88 (77.3) | 59/73 (80.8)
Bacteroides thetaiotaomicron | 36/41 (87.8) | 31/36 (86.1)
Bacteroides uniformis | 12/17 (70.6) | 14/16 (87.5)
Bacteroides vulgatus | 14/16 (87.5) | 4/6 (66.7)
Clostridium perfringens | 18/19 (94.7) | 20/22 (90.9)
Peptostreptococcus micros | 13/17 (76.5) | 8/11 (72.7)
a Two cIAI pivotal studies and two Resistant Pathogen studies; b Includes Streptococcus anginosus, Streptococcus intermedius, and Streptococcus constellatus

14.3 Community-Acquired Bacterial Pneumonia

Tigecycline for injection was evaluated in adults for the treatment of community-acquired bacterial pneumonia (CABP) in two randomized, double-blind, active-controlled, multinational, multicenter studies (Studies 1 and 2). These studies compared tigecycline for injection (100 mg intravenous initial dose followed by 50 mg every 12 hours) with levofloxacin (500 mg intravenous every 12 or 24 hours). In Study 1, after at least 3 days of intravenous therapy, a switch to oral levofloxacin (500 mg daily) was permitted for both treatment arms. Total therapy was 7 to 14 days. Patients with community-acquired bacterial pneumonia who required hospitalization and intravenous therapy were enrolled in the studies. The primary efficacy endpoint was the clinical response at the test of cure (TOC) visit in the co-primary populations of the clinically evaluable (CE) and clinical modified intent-to-treat (c-mITT) patients. See Table 8. Clinical cure rates at TOC by pathogen in the microbiologically evaluable patients are presented in Table 9.

Table 8. Clinical Cure Rates from Two Studies in Community-Acquired Bacterial Pneumonia after 7 to 14 Days of Total Therapy

 | Tigecycline for Injectiona; n/N (%) |  | Levofloxacinb; n/N (%) | 95% CIc
Study 1d
CE |  | 125/138 (90.6) | 136/156 (87.2) | (-4.4, 11.2)
c-mITT |  | 149/191 (78) | 158/203 (77.8) | (-8.5, 8.9)
Study 2
CE |  | 128/144 (88.9) | 116/136 (85.3) | (-5.0, 12.2)
c-mITT |  | 170/203 (83.7) | 163/200 (81.5) | (-5.6, 10.1)
a 100 mg initially, followed by 50 mg every 12 hours
b Levofloxacin (500 mg intravenous every 12 or 24 hours)
c 95% confidence interval for the treatment difference
d After at least 3 days of intravenous therapy, a switch to oral levofloxacin (500 mg daily) was permitted for both treatment arms in Study 1.

Table 9. Clinical Cure Rates By Infecting Pathogen in Microbiologically Evaluable Patients with Community-Acquired Bacterial Pneumoniaa

Pathogen | Tigecycline for Injection; n/N; (%) | Levofloxacin; n/N; (%)
Haemophilus influenzae | 14/17 (82.4) | 13/16 (81.3)
Legionella pneumophila | 10/10 (100.0) | 6/6 (100.0)
Streptococcus pneumoniae; (penicillin-susceptible only)b | 44/46 (95.7) | 39/44 (88.6)
a Two CABP studies
b Includes cases of concurrent bacteremia [cure rates of 20/22 (90.9%) versus 13/18 (72.2%) for tigecycline and levofloxacin respectively]

To further evaluate the treatment effect of tigecycline, a post-hoc analysis was conducted in CABP patients with a higher risk of mortality, for whom the treatment effect of antibacterial drugs is supported by historical evidence. The higher-risk group included CABP patients from the two studies with any of the following factors:

- Age ≥50 years
- PSI score ≥3
- Streptococcus pneumoniae bacteremia

The results of this analysis are shown in Table 10. Age ≥50 was the most common risk factor in the higher-risk group.

Table 10. Post-hoc Analysis of Clinical Cure Rates in Patients with Community-Acquired Bacterial Pneumonia Based on Risk of Mortality a

 |  | Tigecycline for Injection; n/N; (%) | Levofloxacin; n/N; (%) | 95% CIb
Study 1c
CE
Higher risk
Yes | 93/103 (90.3) |  | 84/102 (82.4) | (-2.3, 18.2)
No | 32/35 (91.4) |  | 52/54 (96.3) | (-20.8, 7.1)
c-mITT
Higher risk
Yes | 111/142 (78.2) |  | 100/134 (74.6) | (-6.9, 14)
No | 38/49 (77.6) |  | 58/69 (84.1) | (-22.8, 8.7)
Study 2
CE
Higher risk
Yes | 95/107 (88.8) |  | 68/85 (80) | (-2.2, 20.3)
No | 33/37 (89.2) |  | 48/51 (94.1) | (-21.1, 8.6)
c-mITT
Higher risk
Yes | 112/134 (83.6) |  | 93/120 (77.5) | (-4.2, 16.4)
No | 58/69 (84.1) |  | 70/80 (87.5) | (-16.2, 8.8)
a Patients at higher risk of death include patients with any one of the following: ≥50 year of age; PSI score ≥3; or bacteremia due to Streptococcus pneumoniae
b 95% confidence interval for the treatment difference
c After at least 3 days of intravenous therapy, a switch to oral levofloxacin (500 mg daily) was permitted for both treatment arms in Study 1.

16 HOW SUPPLIED/STORAGE AND HANDLING

Tigecycline for injection, USP is available in a single-dose 5 mL glass vial containing 50 mg tigecycline, USP as an orange lyophilized powder for reconstitution.

It is supplied as:

5 mL glass vial containing 50 mg tigecycline, USP - 10 vials/box. NDC 70121-1647-7

Prior to reconstitution, tigecycline for injection, USP should be stored at 20°C to 25°C (68°F to 77°F); excursions permitted between 15°C to 30°C (59°F to 86°F) [see USP Controlled Room Temperature].

The reconstituted solution of tigecycline for injection, USP may be stored at room temperature (not to exceed 25°C/77°F) for up to 24 hours (up to 6 hours in the vial and the remaining time in the intravenous bag) [see Dosage and Administration (2.5)].

17 PATIENT COUNSELING INFORMATION

Tooth Discoloration and Inhibition of Bone Growth

Advise pregnant women that tigecycline for injection may cause permanent discoloration of deciduous teeth and reversible inhibition of bone growth when administered during the second and third trimesters of pregnancy [see Warnings and Precautions (5.7, 5.8) and Use in Specific Populations (8.1, 8.4)].

Lactation

Advise a woman not to breastfeed for longer than 3 weeks while taking tigecycline for injection because of the lack of data on effects due to prolonged breastfeeding, and the theoretical risk of dental discoloration and inhibition of bone growth. Women may also consider reducing infant exposure through pumping and discarding breastmilk during and for 9 days after the last dose of tigecycline [see Use in Specific Populations (8.2)].

Diarrhea

Advise patients, their families, or caregivers that diarrhea is a common problem caused by antibacterial drugs, including tigecycline for injection. Sometimes, frequent watery or bloody diarrhea may occur and may be a sign of a more serious intestinal infection. If severe watery or bloody diarrhea develops, advise patients to contact his or her healthcare provider [see Warnings and Precautions (5.9)].

Development of Resistance

Patients should be counseled that antibacterial drugs including tigecycline for injection should only be used to treat bacterial infections. They do not treat viral infections (e.g., the common cold). When tigecycline for injection is prescribed to treat a bacterial infection, patients should be told that although it is common to feel better early in the course of therapy, the medication should be taken exactly as directed. Skipping doses or not completing the full course of therapy may (1) decrease the effectiveness of the immediate treatment and (2) increase the likelihood that bacteria will develop resistance and will not be treatable by tigecycline for injection or other antibacterial drugs in the future.

This product’s label may have been updated. For current full prescribing information, please visit: www.amneal.com

Distributed by
Amneal Pharmaceuticals LLC
Bridgewater, NJ 08807

Made in India

Rev. 12-2024-06